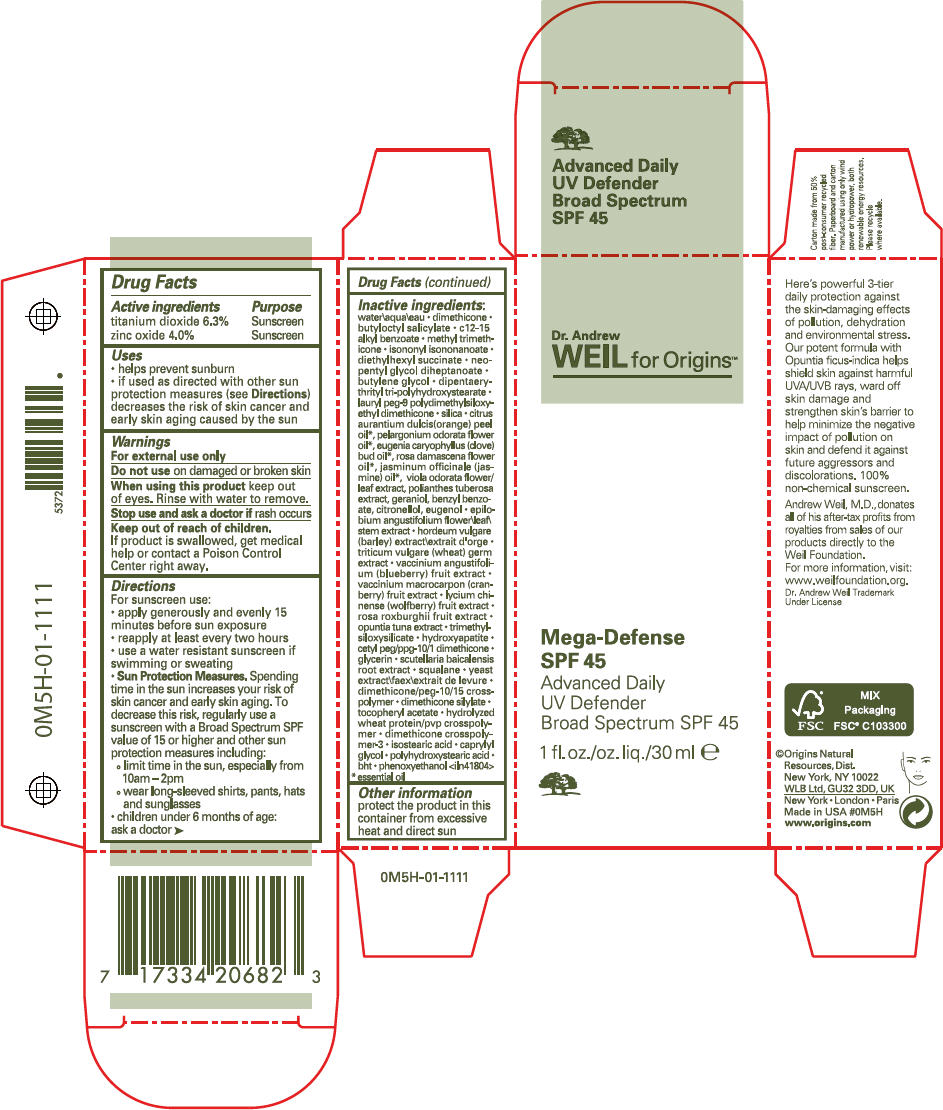 DRUG LABEL: DR ANDREW WEILS FOR ORIGINS
NDC: 59427-113 | Form: LOTION
Manufacturer: ORIGINS NATURAL RESOURCES INC.
Category: otc | Type: HUMAN OTC DRUG LABEL
Date: 20230911

ACTIVE INGREDIENTS: TITANIUM DIOXIDE 63 mg/1 mL; ZINC OXIDE 40 mg/1 mL
INACTIVE INGREDIENTS: WATER; DIMETHICONE; BUTYLOCTYL SALICYLATE; ALKYL (C12-15) BENZOATE; METHYL TRIMETHICONE; ISONONYL ISONONANOATE; DIETHYLHEXYL SUCCINATE; NEOPENTYL GLYCOL DIHEPTANOATE; BUTYLENE GLYCOL; DIPENTAERYTHRITYL TRI-POLYHYDROXYSTEARATE; LAURYL PEG-9 POLYDIMETHYLSILOXYETHYL DIMETHICONE; SILICON DIOXIDE; ORANGE OIL, COLD PRESSED; CLOVE OIL; ROSA X DAMASCENA FLOWER OIL; JASMINUM OFFICINALE FLOWER; VIOLA ODORATA FLOWERING TOP; GERANIOL; BENZYL BENZOATE; .BETA.-CITRONELLOL, (R)-; EUGENOL; EPILOBIUM ANGUSTIFOLIUM FLOWERING TOP; BARLEY; WHEAT GERM; LOWBUSH BLUEBERRY; CRANBERRY; LYCIUM CHINENSE FRUIT; ROSA ROXBURGHII FRUIT; TRIBASIC CALCIUM PHOSPHATE; GLYCERIN; SCUTELLARIA BAICALENSIS ROOT; SQUALANE; YEAST, UNSPECIFIED; .ALPHA.-TOCOPHEROL ACETATE; ISOSTEARIC ACID; CAPRYLYL GLYCOL; BUTYLATED HYDROXYTOLUENE; PHENOXYETHANOL

DR WEILS MEGA-DEFENSE ADVANCED DAILY UV DEFENDER BROAD SPECTRUM SPF 45
SUNCREEN

Drug Facts

ACTIVE INGREDIENT

Active ingredients | Purpose
titanium dioxide 6.3% | Sunscreen
zinc oxide 4.0% | Sunscreen

Uses

- helps prevent sunburn
- if used as directed with other sun protection measures (see Directions) decreases the risk of skin cancer and early skin aging caused by the sun

Warnings

For external use only

Do not use on damaged or broken skin

When using this product keep out of eyes. Rinse with water to remove.

Stop use and ask a doctor if rash occurs

Keep out of reach of children.
If product is swallowed, get medical help or contact a Poison Control Center right away.

Directions

For sunscreen use:

- apply generously and evenly 15 minutes before sun exposure
- reapply at least every two hours
- use a water resistant sunscreen if swimming or sweating
- Sun Protection Measures. Spending time in the sun increases your risk of skin cancer and early skin aging. To decrease this risk, regularly use a sunscreen with a Broad Spectrum SPF value of 15 or higher and other sun protection measures including:
  - limit time in the sun, especially from 10am – 2pm
  - wear long-sleeved shirts, pants, hats and sunglasses
- children under 6 months of age: ask a doctor

Inactive ingredients

water\aqua\eau • dimethicone • butyloctyl salicylate • c12-15 alkyl benzoate • methyl trimethicone • isononyl isononanoate • diethylhexyl succinate • neopentyl glycol diheptanoate • butylene glycol • dipentaerythrityl tri-polyhydroxystearate • lauryl peg-9 polydimethylsiloxyethyl dimethicone • silica • citrus aurantium dulcis(orange) peel oil [essential oil] , pelargonium odorata flower oil , eugenia caryophyllus (clove) bud oil , rosa damascena flower oil , jasminum officinale (jasmine) oil , viola odorata flower/leaf extract, polianthes tuberosa extract, geraniol, benzyl benzoate, citronellol, eugenol • epilobium angustifolium flower\leaf\stem extract • hordeum vulgare (barley) extract\extrait d'orge • triticum vulgare (wheat) germ extract • vaccinium angustifolium (blueberry) fruit extract • vaccinium macrocarpon (cranberry) fruit extract • lycium chinense (wolfberry) fruit extract • rosa roxburghii fruit extract • opuntia tuna extract • trimethylsiloxysilicate • hydroxyapatite • cetyl peg/ppg-10/1 dimethicone • glycerin • scutellaria baicalensis root extract • squalane • yeast extract\faex\extrait de levure • dimethicone/peg-10/15 crosspolymer • dimethicone silylate • tocopheryl acetate • hydrolyzed wheat protein/pvp crosspolymer • dimethicone crosspolymer-3 • isostearic acid • caprylyl glycol • polyhydroxystearic acid • bht • phenoxyethanol <iln41804>

Other information

protect the product in this container from excessive heat and direct sun

PRINCIPAL DISPLAY PANEL - 30 ml Bottle Carton

Dr. Andrew
WEIL for Origins™

Mega-Defense
SPF 45
Advanced Daily
UV Defender
Broad Spectrum SPF 45

1 fl. oz./oz. liq./30 ml e